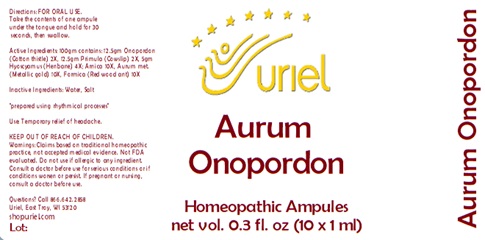 DRUG LABEL: Aurum Onopordon
NDC: 48951-1199 | Form: LIQUID
Manufacturer: Uriel Pharmacy Inc.
Category: homeopathic | Type: HUMAN OTC DRUG LABEL
Date: 20240401

ACTIVE INGREDIENTS: ONOPORDUM ACANTHIUM FLOWER 2 [hp_X]/1 mL; PRIMULA VERIS FLOWER 2 [hp_X]/1 mL; HYOSCYAMUS NIGER LEAF 4 [hp_X]/1 mL; ARNICA MONTANA 10 [hp_X]/1 mL; GOLD 10 [hp_X]/1 mL; FORMICA RUFA 10 [hp_X]/1 mL
INACTIVE INGREDIENTS: WATER; SODIUM CHLORIDE

Aurum Onopordon

INDICATIONS AND USAGE

Directions: FOR ORAL USE.

DOSAGE AND ADMINISTRATION

Take the contents of one ampule under the tongue and hold for 30 seconds, then swallow.

ACTIVE INGREDIENT

Active Ingredients: 100gm contains: 12.5gm Onopordon (Cotton thistle) 2X, 12.5gm Primula (Cowslip) 2X, 5gm Hyoscyamus (Henbane) 4X; Arnica 10X, Aurum met. (Metallic gold) 10X, Formica (Red wood ant) 10X

Inactive Ingredients: Water, Salt

"prepared using rhythmical processes"

PURPOSE

Use: Temporary relief of headache.

KEEP OUT OF REACH OF CHILDREN.

WARNINGS

Warnings: Claims based on traditional homeopathic practice, not accepted medical evidence. Not FDA evaluated. Do not use if allergic to any ingredient. Consult a doctor before use for serious conditions or if conditions worsen or persist. If pregnant or nursing, consult a doctor before use.

QUESTIONS

Questions? Call 866.642.2858 Uriel, East Troy, WI 53120 shopuriel.com Lot: